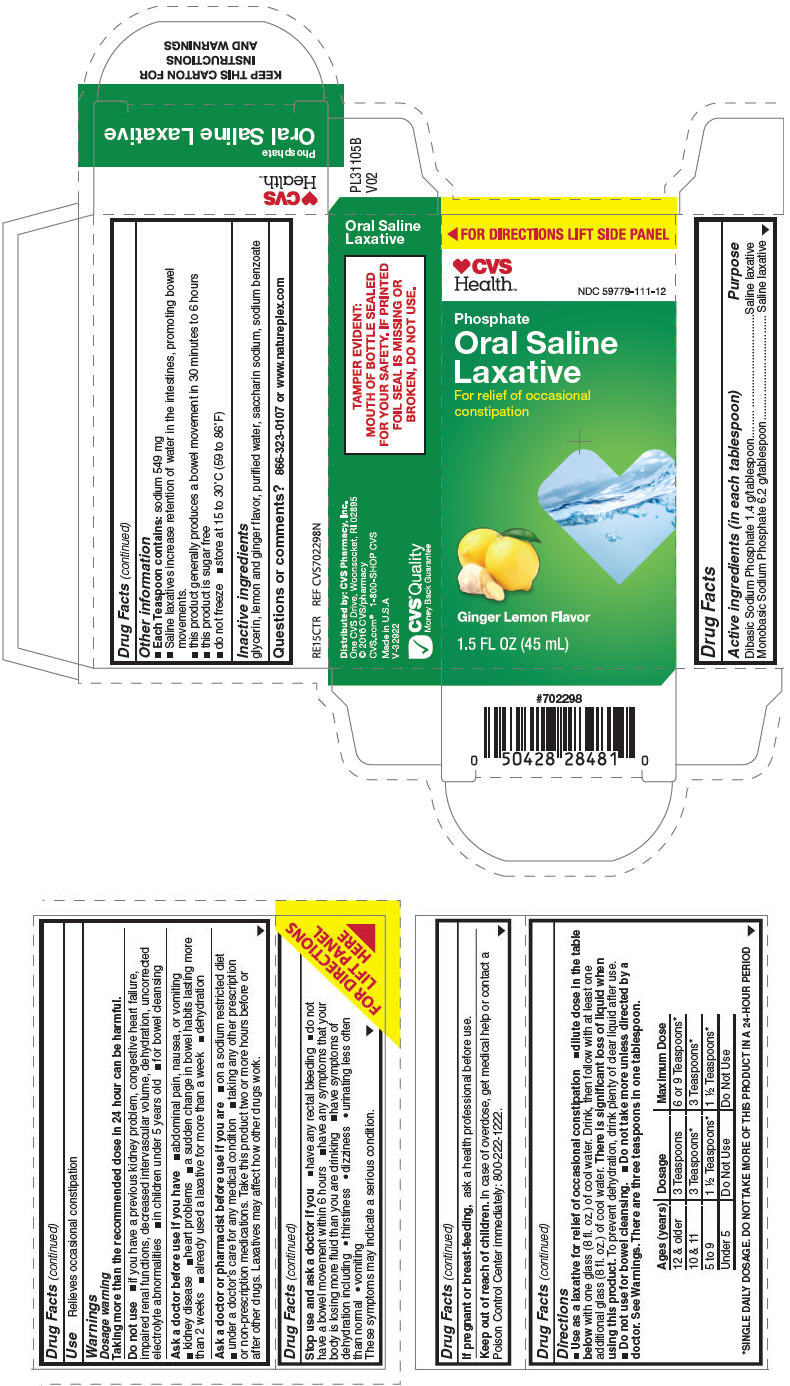 DRUG LABEL: Oral Saline Laxative
NDC: 59779-111 | Form: LIQUID
Manufacturer: CVS Pharmacy
Category: otc | Type: HUMAN OTC DRUG LABEL
Date: 20171227

ACTIVE INGREDIENTS: SODIUM PHOSPHATE, DIBASIC, UNSPECIFIED FORM 1.4 g/14.7868 mL; SODIUM PHOSPHATE, MONOBASIC, UNSPECIFIED FORM 6.2 g/14.7868 mL
INACTIVE INGREDIENTS: GLYCERIN; WATER; SACCHARIN SODIUM; SODIUM BENZOATE

ORAL SALINE LAXATIVE
GINGER LEMON

Drug Facts

ACTIVE INGREDIENT

Active ingredients (in each tablespoon) | Purpose
Dibasic Sodium Phosphate 1.4 g/tablespoon | Saline laxative
Monobasic Sodium Phosphate 6.2 g/tablespoon | Saline laxative

Use

Relieves occasional constipation

Warnings

Dosage warning

Taking more than the recommended dose in 24 hour can be harmful.

Do not use

- if you have a previous kidney problem, congestive heart failure, impaired renal functions, decreased intervascular volume, dehydration, uncorrected electrolyte abnormalities
- in children under 5 years old
- for bowel cleansing

Ask a doctor before use if you have

- abdominal pain, nausea, or vomiting
- kidney disease
- heart problems
- a sudden change in bowel habits lasting more than 2 weeks
- already used a laxative for more than a week
- dehydration

Ask a doctor or pharmacist before use if you are

- on a sodium restricted diet
- under a doctor's care for any medical condition
- taking any other prescription or non-prescription medications. Take this product two or more hours before or after other drugs. Laxatives may affect how other drugs work.

Stop use and ask a doctor if you

- have any rectal bleeding
- do not have a bowel movement within 6 hours
- have any symptoms that your body is losing more fluid than you are drinking
- have symptoms of dehydration including
  - thirstiness
  - dizziness
  - urinating less often than normal
  - vomiting

These symptoms may indicate a serious condition.

PREGNANCY OR BREAST FEEDING

If pregnant or breast-feeding, ask a health professional before use.

Keep out of reach of children. In case of overdose, get medical help or contact a Poison Control Center immediately: 800-222-1222.

Directions

- Use as a laxative for relief of occasional constipation
- dilute dose in the table below with one glass (8 fl. oz.) of cool water. Drink, then follow with at least one additional glass (8 fl. oz.) of cool water. There is significant loss of liquid when using this product. To prevent dehydration, drink plenty of clear liquid after use.
- Do not use for bowel cleansing.
- Do not take more unless directed by a doctor. See Warnings. There are three teaspoons in one tablespoon.

Ages (years) | Dosage | Maximum Dose
12 & older | 3 Teaspoons | 6 or 9 Teaspoons [SINGLE DAILY DOSAGE. DO NOT TAKE MORE OF THIS PRODUCT IN A 24-HOUR PERIOD]
10 & 11 | 3 Teaspoons | 3 Teaspoons
5 to 9 | 1 ½ Teaspoons | 1 ½ Teaspoons
Under 5 | Do Not Use | Do Not Use

Other information

- Each Teaspoon contains: sodium 549 mg
- Saline laxatives increase retention of water in the intestines, promoting bowel movements.
- this product generally produces a bowel movement in 30 minutes to 6 hours
- this product is sugar free
- do not freeze
- store at 15 to 30°C (59 to 86°F)

Inactive ingredients

glycerin, lemon and ginger flavor, purified water, saccharin sodium, sodium benzoate

Questions or comments?

866-323-0107 or www.natureplex.com

Distributed by: CVS Pharmacy, Inc.
One CVS Drive, Woonsocket, RI 02895

PRINCIPAL DISPLAY PANEL - 45 mL Bottle Carton

FOR DIRECTIONS LIFT SIDE PANEL

CVS
Health™

NDC 59779-111-12

Phosphate
Oral Saline
Laxative

For relief of occasional
constipation

Ginger Lemon Flavor

1.5 FL OZ (45 mL)